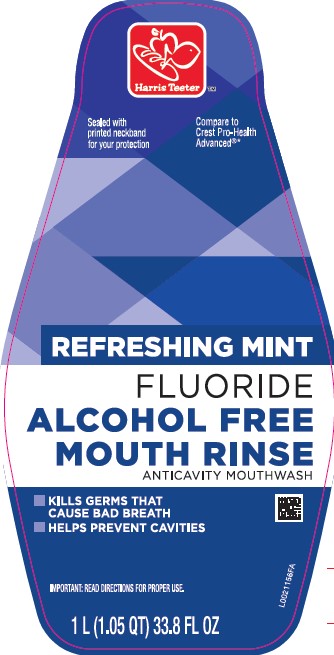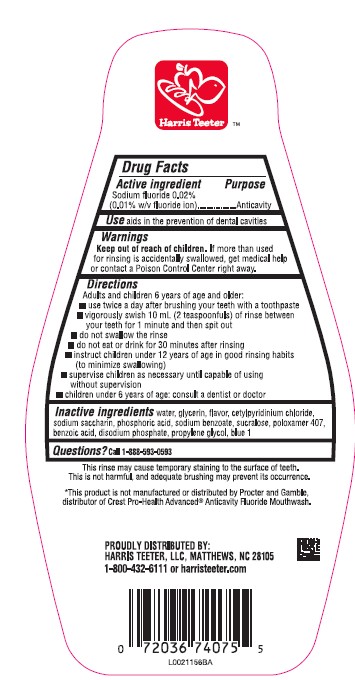 DRUG LABEL: Oral Antivavity
NDC: 72036-576 | Form: MOUTHWASH
Manufacturer: HARRIS TEETER
Category: otc | Type: HUMAN OTC DRUG LABEL
Date: 20260204

ACTIVE INGREDIENTS: SODIUM FLUORIDE 0.1 mg/1 mL
INACTIVE INGREDIENTS: WATER; GLYCERIN; CETYLPYRIDINIUM CHLORIDE; SACCHARIN SODIUM; PHOSPHORIC ACID; SODIUM BENZOATE; SUCRALOSE; POLOXAMER 407; BENZOIC ACID; SODIUM PHOSPHATE, DIBASIC, ANHYDROUS; PROPYLENE GLYCOL; FD&C BLUE NO. 1

Harris Teeter 576.001/576AC-AD
Alcohol Free Fluoride Refreshing Mint Mouthwash

Active ingredient

Sodium fluoride 0.02% (0.01% w/v fluoride ion)

Purpose

Anticavity

Use

aids in the prevention of dental cavities

Warnings

For this product

Keep out of reach of children.

If more than used for rinsing is accidentally swallowed, get medical help or contact a Poison Control Center right away.

Directions

Adults and children 6 years of age and older:

- use twice daily after brushing your teeth with a toothpaste
- vigorously swish 10 mL (2 teaspoonfuls) of rinse bwtween your teeth for 1 minute then spit out
- do not swallow the rinse
- do not eat or drink for 30 minutes after rinsing
- instruct children under 12 years of age in good rinsing habits (to minimize swallowing)
- supervise children as necessary until capable of using witout supervision
- children under 6 years of age: consult a dentist or doctor

Inactive ingredients

water, glycerin, flavor, cetylpyridinium chloride, sodium saccharin, phosphoric acid, sodium benzoate, sucralose, poloxamer 407, benzoic acid, disodium phosphate, propylene glycol, blue 1

Questions?

Call 1-888-593-0593

Claims/Disclaimer

This rinse may cause temporary staining to the surface of teeth.

This is not harmful, and adequate brushing may prevent its occurrence.

*This product is not manufactured or distributed by Proctor and Gamble, distributer of Crest Pro-Health AdvancedAnticavity Fluoride Mouthwash.

Adverse Reactions

PROUDLY DISTRIBUTED BY:

HARRIS TEETER, LLC, MATTHEWS, NC 28105

1-800-432-6111 or harristeeter.com

Principal display panel

Harris Teeter™

Sealed with printed neckband for your protection

Compare to Crest Pro-Health Advanced®*

Refreshing Mint

Fluoride

Alcohol Free

Mouth Rinse

Anticavity Mouthwash

- KILLS GERMS THAT CAUSE BAD BREATH
- HELPS PREVENT CAVITIES

IMPORTANT: READ DIRECTINS FOR PROPER USE

1 L (1.05 QT) 33.8 FL OZ